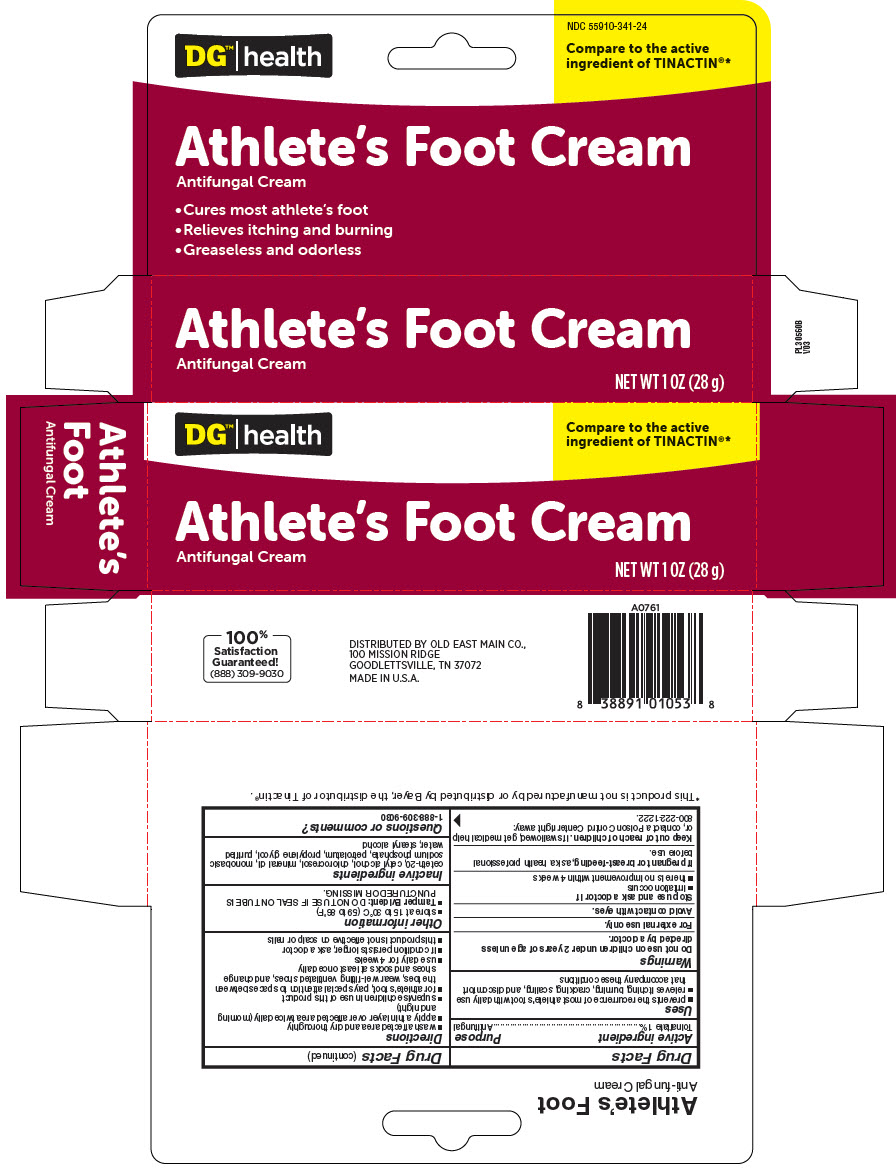 DRUG LABEL: Athletes Foot 
NDC: 55910-341 | Form: CREAM
Manufacturer: Dollar General
Category: otc | Type: HUMAN OTC DRUG LABEL
Date: 20250702

ACTIVE INGREDIENTS: TOLNAFTATE 0.01 mg/10 g
INACTIVE INGREDIENTS: CETETH-20; CETYL ALCOHOL; CHLOROCRESOL; MINERAL OIL; PETROLATUM; PROPYLENE GLYCOL; WATER; SODIUM PHOSPHATE, MONOBASIC, ANHYDROUS; STEARYL ALCOHOL

Athlete's Foot Cream
Antifungal Cream

Drug Facts

Active ingredient

Tolnaftate 1%

Purpose

Antifungal

Uses

- prevents the recurrence of most athlete's foot with daily use
- relieves itching, burning, cracking, scaling, and discomfort that accompany these conditions

Warnings

Do not use on children under 2 years of age unless directed by a doctor.

For external use only.

Avoid contact with eyes.

Stop use and ask a doctor if

- irritation occurs
- there is no improvement within 4 weeks

PREGNANCY OR BREAST FEEDING

If pregnant or breast-feeding, ask a health professional before use.

Keep out of reach of children. If swallowed, get medical help or, contact a Poison Control Center right away: 800-222-1222.

Directions

- wash affected area and dry thoroughly
- apply a thin layer over affected area twice daily (morning and night)
- supervise children in use of this product
- for athlete's foot, pay special attention to spaces between the toes, wear well-fitting ventilated shoes, and change shoes and socks at least once daily
- use daily for 4 weeks
- if condition persists longer, ask a doctor
- this product is not effective on scalp or nails

Other information

- store at 15 to 30°C (59 to 86°F)
- Tamper Evident: DO NOT USE IF SEAL ON TUBE IS PUNCTURED OR MISSING.

Inactive ingredients

ceteth-20, cetyl alcohol, chlorocresol, mineral oil, monobasic sodium phosphate, petrolatum, propylene glycol, purified water, stearyl alcohol

Questions or comments?

1-888-309-9030

DISTRIBUTED BY OLD EAST MAIN CO.,
100 MISSION RIDGE
GOODLETTSVILLE, TN 37072

PRINCIPAL DISPLAY PANEL - 28 g Tube Carton

DG™| health

Compare to the active
ingredient of TINACTIN®*

Athlete's Foot Cream
Antifungal Cream

NET WT 1 OZ (28 g)